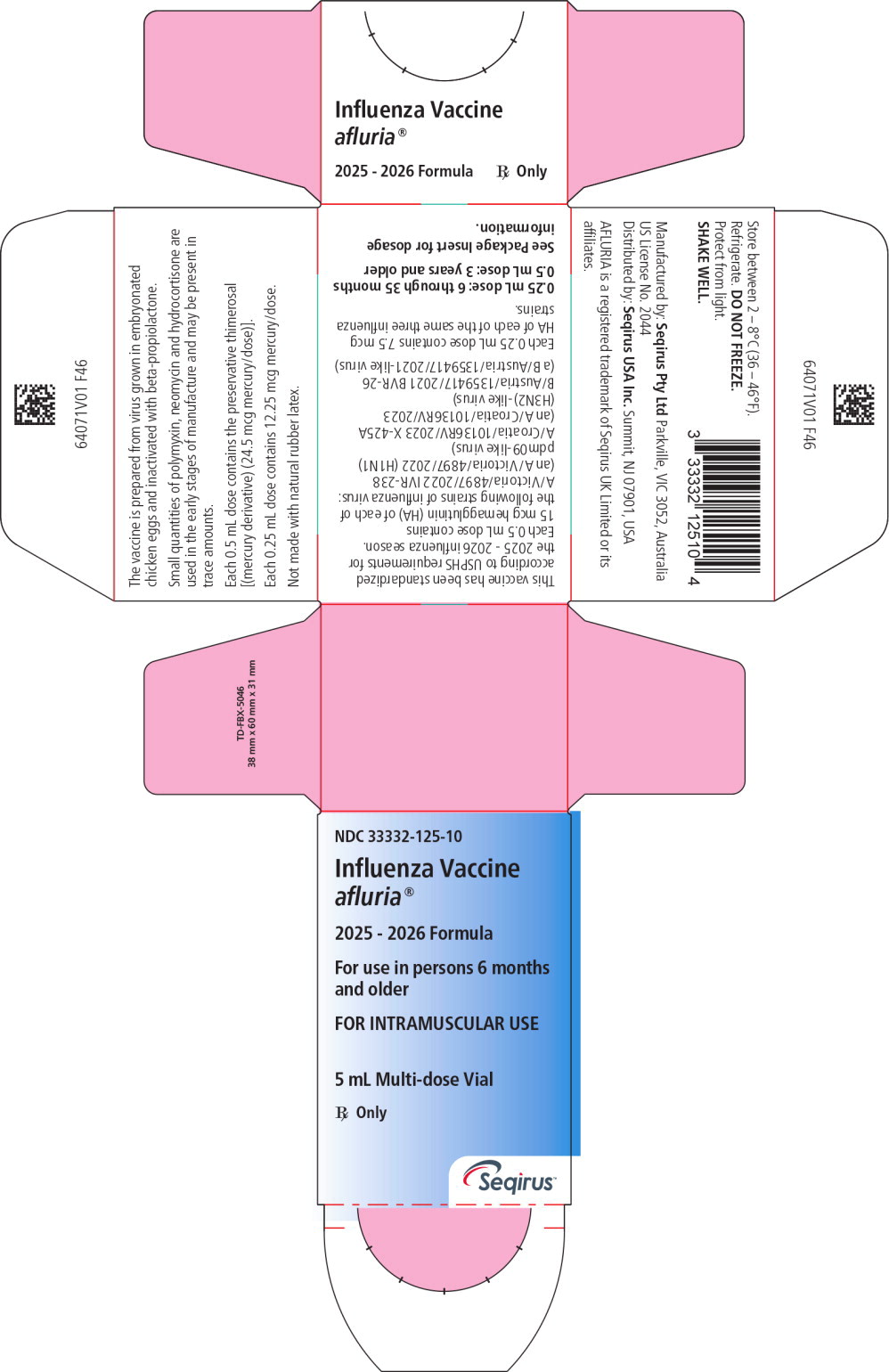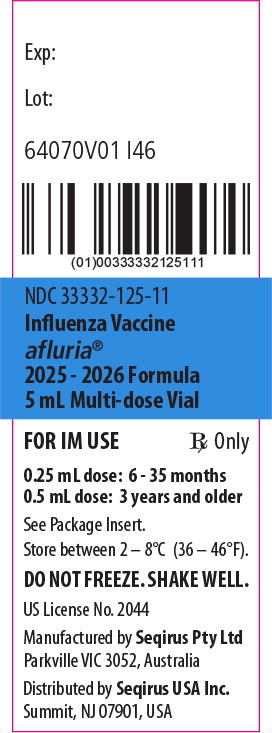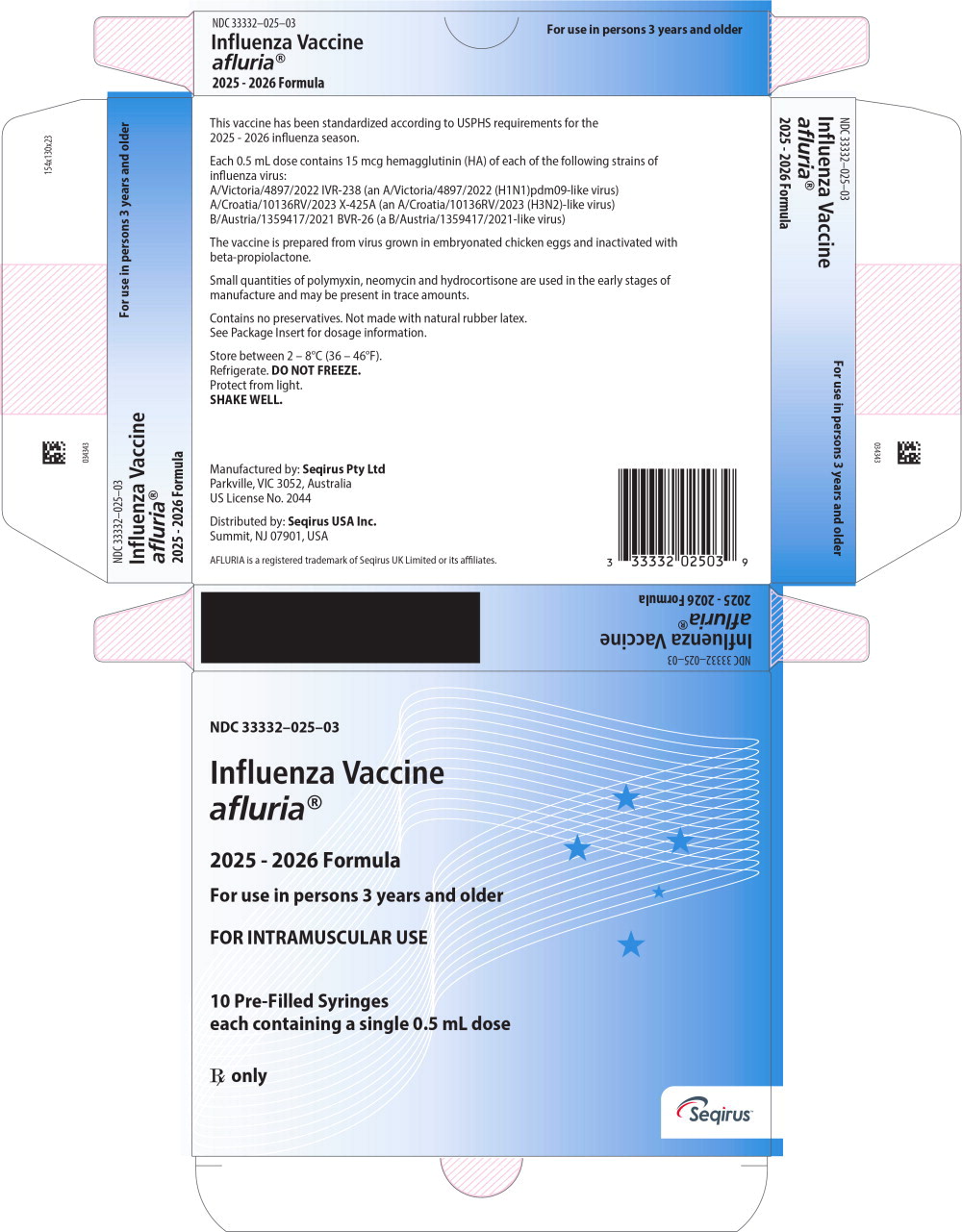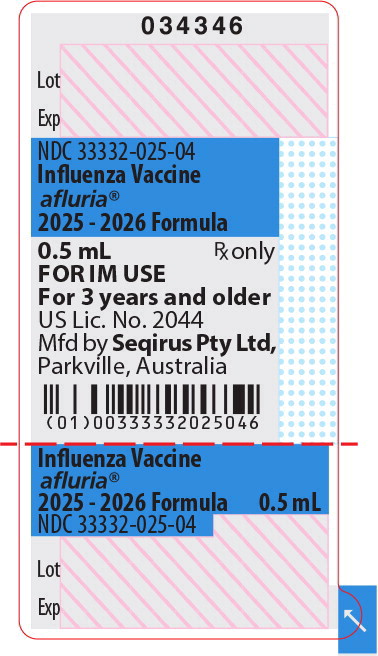 DRUG LABEL: Afluria
NDC: 33332-125 | Form: INJECTION, SUSPENSION
Manufacturer: Seqirus PTY LTD.
Category: other | Type: VACCINE LABEL
Date: 20250617

ACTIVE INGREDIENTS: INFLUENZA A VIRUS A/Victoria/4897/2022 IVR-238 (H1N1) ANTIGEN (PROPIOLACTONE INACTIVATED) 15 ug/0.5 mL; INFLUENZA A VIRUS A/Croatia/10136RV/2023 X-425A (H3N2) ANTIGEN (PROPIOLACTONE INACTIVATED) 15 ug/0.5 mL; INFLUENZA B VIRUS B/Austria/1359417/2021 BVR-26 ANTIGEN (PROPIOLACTONE INACTIVATED) 15 ug/0.5 mL
INACTIVE INGREDIENTS: SODIUM CHLORIDE 4.1 mg/0.5 mL; SODIUM PHOSPHATE, MONOBASIC, DIHYDRATE 80 ug/0.5 mL; SODIUM PHOSPHATE, DIBASIC, ANHYDROUS 300 ug/0.5 mL; POTASSIUM PHOSPHATE, MONOBASIC 20 ug/0.5 mL; POTASSIUM CHLORIDE 20 ug/0.5 mL; CALCIUM CHLORIDE 0.5 ug/0.5 mL; THIMEROSAL 24.5 ug/0.5 mL; WATER

HIGHLIGHTS OF PRESCRIBING INFORMATION

These highlights do not include all the information needed to use AFLURIA® safely and effectively. See full prescribing information for AFLURIA.
AFLURIA (Influenza Vaccine)
Injectable Suspension, for Intramuscular Use
2025-2026 Formula
Initial U.S. Approval: 2007

1 INDICATIONS AND USAGE

- · AFLURIA is an inactivated influenza vaccine indicated for active immunization for the prevention of disease caused by influenza A subtype viruses and type B virus contained in the vaccine. (1)
- AFLURIA is approved for use in persons 6 months of age and older. (1)

2 DOSAGE AND ADMINISTRATION

For intramuscular use, by needle and syringe (6 months and older) or by PharmaJet® Stratis® Needle-Free Injection System (18 through 64 years). (2)

Age | Dose | Schedule
6 months through 35 months | One or two dosesa, 0.25 mL each | If 2 doses, administer at least 1 month apart
36 months through 8 years | One or two dosesa, 0.5 mL each | If 2 doses, administer at least 1 month apart
9 years and older | One dose, 0.5 mL | Not Applicable
a1 or 2 doses depends on vaccination history as per Advisory Committee on Immunization Practices annual recommendations on prevention and control of influenza with vaccines. (2)

3 DOSAGE FORMS AND STRENGTHS

AFLURIA is an injectable suspension. A single dose is 0.25 mL or 0.5 mL depending on age. (3)

4 CONTRAINDICATIONS

- Do not administer AFLURIA to anyone with a history of a severe allergic reaction (e.g., anaphylaxis) to any component of the vaccine including egg protein, or to a previous dose of any influenza vaccine (4, 11).

5 WARNINGS AND PRECAUTIONS

- If Guillain-Barré Syndrome (GBS) has occurred within 6 weeks of previous influenza vaccination, the decision to give AFLURIA should be based on careful consideration of the potential benefits and risks. (5.1)

6 ADVERSE REACTIONS

Administered by needle and syringe (AFLURIA QUADRIVALENT data):

- In adults 18 through 64 years, the most commonly reported injection-site adverse reaction was pain (≥ 40%). The most common systemic adverse reactions were myalgia and headache (≥ 20%). (6.1)
- In adults 65 years of age and older, the most commonly reported injection-site adverse reaction was pain (≥ 20%). The most common systemic adverse reaction was myalgia (≥ 10%). (6.1)
- In children 6 months through 35 months of age, the most commonly reported injection-site reactions were pain and redness (≥ 20%).The most common systemic adverse reactions were irritability (≥ 30%), diarrhea and loss of appetite (≥ 20%). (6.1)
- In children 36 through 59 months of age, the most commonly reported injection site reactions were pain (≥ 30%) and redness (≥ 20%). The most commonly reported systemic adverse reactions were malaise and fatigue, and diarrhea (≥ 10%). (6.1)
- In children 5 through 8 years, the most commonly reported injection-site adverse reactions were pain (≥ 50%), redness and swelling (≥ 10%). The most common systemic adverse reaction was headache (≥ 10%). (6.1)
- In children 9 through 17 years, the most commonly reported injection-site adverse reactions were pain (≥ 50%), redness and swelling (≥ 10%). The most common systemic adverse reactions were headache, myalgia, and malaise and fatigue (≥ 10%). (6.1)

Administered by the PharmaJet Stratis Needle-Free Injection System:

- In adults 18 through 64 years of age, the most commonly reported injection-site adverse reactions were tenderness (≥ 80%), swelling, pain, redness (≥ 60%), itching (≥ 20%) and bruising (≥ 10%). The most common systemic adverse reactions were myalgia, malaise (≥ 30%), and headache (≥ 20%). (6.1)

To report SUSPECTED ADVERSE REACTIONS, contact Seqirus USA Inc. at 1-855-358-8966 or VAERS at 1-800-822-7967 or www.vaers.hhs.gov.

8 USE IN SPECIFIC POPULATIONS

- Antibody responses were lower in geriatric subjects than in younger adults. (8.5)

FULL PRESCRIBING INFORMATION

1 INDICATIONS AND USAGE

AFLURIA® is an inactivated influenza vaccine indicated for active immunization for the prevention of disease caused by influenza A subtype viruses and type B virus contained in the vaccine.

AFLURIA is approved for use in persons 6 months of age and older.

2 DOSAGE AND ADMINISTRATION

For intramuscular use:

- By needle and syringe (6 months of age and older)
- By PharmaJet® Stratis® Needle-Free Injection System (18 through 64 years of age)

The dose and schedule for AFLURIA are presented in Table 1.

Table 1: AFLURIA Dosage and Schedule
Age | Dose | Schedule
6 months through 35 months | One or two doses a, 0.25 mL each | If 2 doses, administer at least 1 month apart
36 months through 8 years | One or two doses a, 0.5 mL each | If 2 doses, administer at least 1 month apart
9 years and older | One dose, 0.5mL | Not Applicable
a 1 or 2 doses depends on vaccination history as per Advisory Committee on Immunization Practices annual recommendations on prevention and control of influenza with vaccines.

Immediately before use, shake thoroughly and inspect visually. Parenteral drug products should be inspected visually for particulate matter and discoloration prior to administration, whenever solution and container permit. If either of these conditions exists, the vaccine should not be administered.

When using the single-dose pre-filled syringe, shake the syringe thoroughly and administer the dose immediately.

When using the multi-dose vial, shake the vial thoroughly before withdrawing each dose, and administer the dose immediately. The number of needle punctures should not exceed 20 per multi-dose vial.

- Needle and Syringe: Draw up the dose using a separate sterile needle and syringe for each patient.
- PharmaJet Stratis Needle-Free Injection System: For instructions on withdrawal of a 0.5 mL dose and use of the PharmaJet Stratis Needle-Free Injection System, refer to the Instructions For Use for the PharmaJet Stratis Needle-Free Injection System.

3 DOSAGE FORMS AND STRENGTHS

AFLURIA is an injectable suspension. A single dose is 0.25 mL (for persons 6 through 35 months of age) or 0.5 mL (for persons 36 months of age and older).

4 CONTRAINDICATIONS

Do not administer AFLURIA to anyone with a history of a severe allergic reaction (e.g., anaphylaxis) to any component of the vaccine including egg protein, or to a previous dose of any influenza vaccine (see Description [11]).

5 WARNINGS AND PRECAUTIONS

5.1 Guillain-Barré Syndrome

If Guillain-Barré Syndrome (GBS) has occurred within 6 weeks of previous influenza vaccination, the decision to give AFLURIA should be based on careful consideration of the potential benefits and risks.

The 1976 swine influenza vaccine was associated with an increased frequency of GBS. Evidence for a causal relation of GBS with subsequent vaccines prepared from other influenza viruses is unclear. If influenza vaccine does pose a risk, it is probably slightly more than one additional case per 1 million persons vaccinated.

5.2 Preventing and Managing Allergic Reactions

Appropriate medical treatment must be immediately available to manage potential anaphylactic reactions following administration of AFLURIA.

5.3 Altered Immunocompetence

If AFLURIA is administered to immunocompromised persons, including those receiving immunosuppressive therapy, the immune response may be diminished.

5.4 Limitations of Vaccine Effectiveness

Vaccination with AFLURIA may not protect all individuals.

6 ADVERSE REACTIONS

Data for AFLURIA QUADRIVALENT are relevant to AFLURIA because both vaccines are manufactured using the same process and have overlapping compositions.

In adults 18 through 64 years of age, the most commonly reported injection-site adverse reaction observed in clinical studies with AFLURIA QUADRIVALENT administered by needle and syringe was pain (≥ 40%). The most common systemic adverse reactions observed were myalgia and headache (≥ 20%).

In adults 65 years of age and older, the most commonly reported injection-site adverse reaction observed in clinical studies with AFLURIA QUADRIVALENT administered by needle and syringe was pain (≥ 20%). The most common systemic adverse reaction observed was myalgia (≥ 10%).

In children 6 months through 35 months of age, the most frequently reported injection site reactions in the clinical study with AFLURIA QUADRIVALENT administered by needle and syringe were pain and redness (≥ 20%). The most common systemic adverse reactions were irritability (≥ 30%), diarrhea and loss of appetite (≥ 20%).

In children 36 through 59 months of age, the most commonly reported injection site reactions when AFLURIA QUADRIVALENT was administered by needle and syringe were pain (≥ 30%) and redness (≥ 20%). The most commonly reported systemic adverse reactions were malaise and fatigue, and diarrhea (≥ 10%).

In children 5 through 8 years, the most commonly reported injection-site adverse reactions when AFLURIA QUADRIVALENT was administered by needle and syringe were pain (≥ 50%) and redness and swelling (≥ 10%). The most common systemic adverse reaction was headache (≥ 10%).

In children 9 through 17 years, the most commonly reported injection-site adverse reactions when AFLURIA QUADRIVALENT was administered by needle and syringe were pain (≥ 50%) and redness and swelling (≥ 10%). The most common systemic adverse reactions were headache, myalgia, and malaise and fatigue (≥ 10%).

In adults 18 through 64 years of age, the most commonly reported injection-site adverse reactions observed in a clinical study with AFLURIA using the PharmaJet Stratis Needle-Free Injection System were tenderness (≥ 80%), swelling, pain, redness (≥ 60%), itching (≥ 20%) and bruising (≥ 10%). The most common systemic adverse reactions were myalgia, malaise (≥ 30%) and headache (≥ 20%).

6.1 Clinical Trials Experience

Because clinical studies are conducted under widely varying conditions, adverse reaction rates observed in the clinical studies of a vaccine cannot be directly compared to rates in the clinical studies of another vaccine and may not reflect the rates observed in clinical practice.

Adults

Clinical safety data for AFLURIA QUADRIVALENT in adults have been collected in one clinical trial, Study 1 (NCT02214225), a randomized, double-blind, active-controlled trial conducted in the U.S. in 3449 subjects ages 18 years and older. Subjects in the safety population received one dose of either AFLURIA QUADRIVALENT (N=1721) or one of two formulations of AFLURIA (TIV-1 N=864 or TIV-2 N=864) each containing an influenza type B virus that corresponded to one of the two B viruses in AFLURIA QUADRIVALENT (a type B virus of the Yamagata lineage or a type B virus of the Victoria lineage), respectively. The mean age of the population was 58 years, 57% were female, and racial groups consisted of 82% White, 16% Black, and 2% other; 5% of subjects were Hispanic/Latino. The age sub-groups were 18 through 64 years and 65 years and older with mean ages of 43 years and 73 years, respectively. In this study, AFLURIA QUADRIVALENT and AFLURIA were administered by needle and syringe (see Clinical Studies [14.2]).

Local (injection-site) adverse reactions and systemic adverse reactions were solicited for 7 days post-vaccination (Table 2). Injection site cellulitis, cellulitis-like reactions (defined as concurrent Grade 3 pain, redness, and swelling/lump), and Grade 3 swelling/lump were monitored for 28 days post-vaccination. Unsolicited adverse events were collected for 28 days post-vaccination. Serious adverse events (SAEs), including deaths, were collected for 180 days post-vaccination.

Table 2: Proportion of Subjects Per Age Cohort with Any Solicited Local Adverse Reactions or Systemic Adverse Reactions within 7 Days after Administration of AFLURIA QUADRIVALENT or AFLURIA (TIV-1 or TIV-2) (Study 1) a
 | Percentage (%) b of Subjects in each Age Cohort Reporting a Reaction
 | Subjects 18 through 64 years |  |  |  |  |  | Subjects ≥ 65 years
 | AFLURIA Quadrivalent N=854 c |  | AFLURIA (TIV-1) N=428 c |  | AFLURIA (TIV-2) N=430 c |  | AFLURIA Quadrivalent N=867 c |  | AFLURIA (TIV-1) N=436 c |  | AFLURIA (TIV-2) N=434 c
 | Any | Gr 3 | Any | Gr 3 | Any | Gr 3 | Any | Gr 3 | Any | Gr 3 | Any | Gr 3
Local Adverse Reactions d
Pain | 47.9 | 0.7 | 43.7 | 1.4 | 50.7 | 1.2 | 24.6 | 0.1 | 22.7 | 0 | 21.0 | 0.2
Swelling/Lump | 3.7 | 0.1 | 2.3 | 0 | 3.5 | 0.2 | 3.2 | 0.5 | 1.8 | 0 | 1.6 | 0
Redness | 2.9 | 0 | 2.8 | 0 | 2.8 | 0 | 4.2 | 0.3 | 2.1 | 0 | 2.5 | 0.2
Systemic Adverse Reactions e
Myalgia (muscle ache) | 25.5 | 1.9 | 23.4 | 1.4 | 24.2 | 1.2 | 12.7 | 0.3 | 14.0 | 0.7 | 12.2 | 0.5
Headache | 21.7 | 1.7 | 15.2 | 0.9 | 19.1 | 1.2 | 8.4 | 0 | 7.1 | 0.2 | 7.8 | 0.7
Malaise | 8.9 | 0.7 | 9.1 | 0 | 9.3 | 0.7 | 4.4 | 0.5 | 5.0 | 0.2 | 5.1 | 0.2
Nausea | 6.9 | 0.6 | 7.7 | 0.5 | 6.3 | 1.2 | 1.6 | 0 | 1.8 | 0 | 2.1 | 0.2
Chills | 4.8 | 0.6 | 4.4 | 0.2 | 4.7 | 0.5 | 2.0 | 0 | 2.1 | 0.5 | 1.4 | 0.2
Vomiting | 1.5 | 0.4 | 0.9 | 0 | 2.3 | 0.7 | 0.5 | 0.1 | 0 | 0 | 0.7 | 0.2
Fever | 1.1 | 0.4 | 0.9 | 0 | 0.5 | 0 | 0.2 | 0 | 0.9 | 0 | 0.5 | 0.2
Abbreviations: Gr 3, Grade 3.
a NCT02214225
b Proportion of subjects reporting each solicited local adverse reaction or systemic adverse reaction by study vaccine group based on the number of subjects contributing any follow up safety information for at least one data value of an individual sign/symptom.
c N = number of subjects in the Safety Population for each study vaccine group.
d Local adverse reactions: Grade 3 pain is that which prevents daily activity; Swelling/Lump and redness: any = ≥ 20mm diameter, Grade 3 = ≥ 100mm diameter.
e Systemic adverse reactions: Fever: any = ≥ 100.4°F (Oral), Grade 3 = ≥ 102.2°F (Oral); Grade 3 for all other adverse reactions is that which prevents daily activity.

In the 28 days following vaccination, no subject experienced cellulitis or a cellulitis-like reaction. All Grade 3 swelling/lump reactions began within 7 days of vaccination and are included in Table 2.

In the 28 days following vaccination, 20.5%, 20.1%, and 20.7% of adults 18 through 64 years and 20.3%, 24.1%, and 20.0% of adults ≥ 65 years who received AFLURIA QUADRIVALENT, AFLURIA TIV-1, and AFLURIA TIV-2, respectively, reported unsolicited adverse events. Rates of individual events were similar between treatment groups, and most events were mild to moderate in severity.

In the 180 days following vaccination, 2.3%, 1.6%, and 1.5% of all subjects who received AFLURIA QUADRIVALENT, AFLURIA TIV-1 and AFLURIA TIV-2 respectively, experienced SAEs, including six deaths, five in the AFLURIA QUADRIVALENT group and one in the AFLURIA TIV-2 group. The majority of SAEs occurred after Study Day 28 and in subjects ≥ 65 years of age who had co-morbid illnesses. No SAEs or deaths appeared related to the study vaccines.

The clinical safety of AFLURIA was also evaluated in a randomized, observer blind, placebo controlled study that included 15,020 subjects 18 through 64 years of age (Study 2; NCT00562484) who were randomized to receive AFLURIA (n=10,015) or placebo (n=5,005) (see Clinical Studies [14.1]). In the 180 days following vaccination in this study, no vaccine-related deaths or vaccine-related SAEs were reported.

Safety information has also been collected in a clinical study of AFLURIA administered using the PharmaJet Stratis Needle-Free Injection System (Study 3; NCT01688921) (see Clinical Studies [14.3]). Study 3 included 1,247 subjects for safety analysis, ages 18 through 64 years, randomized to receive AFLURIA by either the PharmaJet Stratis Needle-Free Injection System (624 subjects) or needle and syringe (623 subjects). No deaths or vaccine-related serious adverse events were reported in Study 3. Local (injection-site) adverse reactions and systemic adverse reactions were solicited for 7 days post-vaccination (Table 3).

Table 3: Proportion of Subjects 18 through 64 Years of Age with Solicited Local Adverse Reactions or Systemic Adverse Reactions within 7 Days after Administration of AFLURIA by PharmaJet Stratis Needle-Free Injection System or Needle and Syringe (Study 3) a
 | Percentage b of Subjects Reporting a Reaction
 | Subjects 18 through 64 years
 | AFLURIA
 | PharmaJet Stratis Needle-Free Injection System N=540-616 c |  | Needle and Syringe N=599-606 c
 | Any | Grade 3 | Any | Grade 3
Local Adverse Reactions d
Tenderness | 89.4 | 2.1 | 77.9 | 1.0
Swelling | 64.8 | 1.7 | 19.7 | 0.2
Pain | 64.4 | 0.8 | 49.3 | 0.7
Redness | 60.1 | 1.3 | 19.2 | 0.3
Itching f | 28.0 | 0.0 | 9.5 | 0.2
Bruising | 17.6 | 0.2 | 5.3 | 0.0
Systemic Adverse Reactions e
Myalgia | 36.4 | 0.8 | 35.5 | 1.0
Malaise | 31.2 | 0.7 | 28.4 | 0.5
Headache | 24.7 | 1.3 | 22.1 | 1.3
Chills | 7.0 | 0.2 | 7.2 | 0.2
Nausea | 6.6 | 0.2 | 6.5 | 0.0
Vomiting | 1.3 | 0.0 | 1.8 | 0.2
Fever | 0.3 | 0.0 | 0.3 | 0.0
a NCT01688921
b Proportion of subjects reporting each local adverse reaction or systemic adverse reaction by treatment group based on the number of subjects contributing at least one data value for an individual sign/symptom (individual reaction denominators).
c N = number of subjects in the Safety Population for each treatment group. Denominators for the PharmaJet Stratis Needle-Free Injection System group were: N=540 for itching and N=605-616 for all other parameters. Denominators for the needle and syringe group were: N=527 for itching and N=599-606 for all other parameters.
d Local adverse reactions: Grade 3 is pain, tenderness or itching that prevents daily activity; Swelling, redness or bruising: any = ≥ 25mm diameter, Grade 3 = > 100mm diameter.
e Systemic adverse reactions: Fever: any = ≥ 100.4°F (Oral), Grade 3 = ≥ 102.2°F (Oral); Grade 3 for all other adverse reactions is that which prevents daily activity.
f A total of 155 subjects (approximately randomly distributed between PharmaJet Stratis Needle-Free Injection System and needle and syringe groups) received Diary Cards without itching listed as a solicited symptom.

In adults 18 through 64 years who received AFLURIA administered by PharmaJet Stratis Needle-Free Injection System, commonly reported unsolicited adverse events were headache (4.2%), injection site hematoma (1.8%), injection site erythema (1.1%), myalgia (1.0%) and nausea (1.0%).

Children 6 Months Through 59 Months of Age

Clinical safety data for AFLURIA QUADRIVALENT in infants and young children have been collected in one clinical trial, Study 4 (NCT02914275), a randomized, observer-blind, comparator-controlled trial conducted in the U.S. in 2247 subjects aged 6 through 59 months. Subjects were stratified into one of two age cohorts of 6 through 35 months or 36 through 59 months (41.6% and 58.4% of the study population, respectively). The mean age of the population was 36.6 months, 51.6% were male, and racial groups consisted of 71.0% White, 21.5% Black, 1.1% Asian, 0.7% Native Hawaiian/Pacific Islander, and 0.3% American Indian/Native American; 26.4% of subjects were Hispanic/Latino. The mean ages of subjects 6 through 35 months and 36 through 59 months were 21.7 months and 47.1 months, respectively. Subjects in the safety population (N=2232) received either AFLURIA QUADRIVALENT (N=1673) or a U.S.-licensed comparator quadrivalent influenza vaccine (N=559). Study subjects were scheduled to receive either a single vaccination or two vaccinations 28 days apart based on their previous vaccination history. In this study, AFLURIA QUADRIVALENT and comparator vaccine were administered by needle and syringe (see Clinical Studies [14.4]).

Local (injection site) adverse reactions and systemic adverse reactions were solicited for 7 days post-vaccination. Cellulitis-like reactions (defined as concurrent Grade 3 pain, redness, and swelling/lump) at the injection site were monitored for 28 days post-vaccination. Subjects were instructed to report and return to clinic within 24 hours in the event of a cellulitis-like reaction. Unsolicited adverse events were collected for 28 days post-vaccination, and SAEs for 6 months following the last vaccination. All solicited local adverse reactions and systemic adverse reactions following any vaccination (first or second dose) are presented in Table 4.

Table 4: Proportion of Subjects Per Age Cohort with Any Solicited Local Adverse Reactions or Systemic Adverse Reactions within 7 Days after Administration of AFLURIA QUADRIVALENT or Comparator QIV (Study 4) a
 | Percentage (%) b of Subjects in each Age Cohort Reporting a Reaction
 | 6 through 35 months |  |  |  | 36 through 59 months
 | AFLURIA Quadrivalent N=668-669 c |  | Comparator N=226-227 c |  | AFLURIA Quadrivalent N=947-949 c |  | Comparator N=317-318 c
 | Any | Gr 3 | Any | Gr 3 | Any | Gr 3 | Any | Gr 3
Local Adverse Reactions d
Pain | 20.8 | 0.1 | 25.6 | 0.4 | 35.5 | 0 | 31.4 | 0.6
Redness | 20.8 | 0.6 | 17.6 | 1.8 | 22.4 | 2.3 | 20.8 | 5.3
Swelling/Lump | 6.1 | 0.4 | 6.2 | 0.9 | 10.1 | 1.7 | 12.9 | 2.5
Systemic Adverse Reactions e
Irritability | 32.9 | 0.7 | 28.2 | 0.4 | - | - | - | -
Diarrhea | 24.2 | 0.1 | 25.6 | 0.4 | 12.1 | 0.1 | 8.8 | 0.6
Loss of Appetite | 20.0 | 0.3 | 19.4 | 0.4 | - | - | - | -
Malaise and Fatigue | - | - | - | - | 14.3 | 0.5 | 13.2 | 0.3
Myalgia | - | - | - | - | 9.9 | 0.1 | 9.4 | 0
Nausea and/or vomiting | 9.4 | 0.7 | 11.0 | 0 | 9.2 | 0.4 | 6.6 | 0.3
Headache | - | - | - | - | 6.2 | 0.4 | 5.0 | 0
Fever f | 7.2 | 2.5 | 11.9 | 2.6 | 4.8 | 1.2 | 6.0 | 0.9
Abbreviations: Gr 3, Grade 3 (severe); Comparator, Comparator quadrivalent influenza vaccine [Fluzone® Quadrivalent (Sanofi Pasteur)]
a NCT02914275
b Percent (%) is derived from the number of subjects that reported the reaction divided by the number of subjects in the Solicited Safety Population with non-missing data for each age cohort, treatment group, and each solicited parameter.
c N = number of subjects in the Solicited Safety Population (subjects who were vaccinated and provided any solicited safety data) for each study vaccine group.
d Local adverse reactions: Grade 3 pain is that which prevents daily activity (36 through 59 month subjects); or cried when limb was moved or spontaneously painful (6 through 35 month subjects); Swelling/Lump and redness: any = ≥ 0mm diameter, Grade 3 = ≥ 30mm diameter.
e Systemic adverse reactions: Fever: any = ≥ 99.5°F (Axillary), Grade 3 = ≥ 101.3°F (Axillary); Grade 3 for all other adverse reactions is that which prevents daily activity; Irritability, Loss of Appetite, Malaise and Fatigue, Myalgia and Headache are age specific systemic adverse reactions, where “-” denotes reaction was not applicable to that age cohort.
f Prophylactic antipyretics (acetaminophen or ibuprophen-containing medications) were not permitted. Antipyretics used to treat fever were permitted and rates of use were as follows: 6 through 35 months (Afluria QIV 5.9%, Comparator QIV 9.0%); 36 through 59 months (Afluria QIV 3.7%, Comparator QIV 2.5%).

In subjects 6 through 35 months of age, all solicited local adverse reactions and systemic adverse reactions were reported at lower frequencies after the second vaccination than after the first vaccination with AFLURIA QUADRIVALENT.

In subjects 36 through 59 months of age, all solicited local adverse reactions and systemic adverse reactions were reported at lower frequencies after the second vaccination than after the first vaccination with AFLURIA QUADRIVALENT.

The most commonly reported unsolicited adverse events in the 28 days following the first or second dose of AFLURIA QUADRIVALENT in subjects 6 through 35 months of age were rhinorrhea (11.2%), cough (10.4%), pyrexia (6.3%), upper respiratory tract infection (4.8%), diarrhea (3.7%), otitis media (2.4%), vomiting (2.4%), nasal congestion (2.4%), nasopharyngitis (1.9%), irritability (1.7%), ear infection (1.6%), croup infectious (1.4%), teething (1.3%), rash (1.2%), influenza like illness (1.0%) and fatigue (1.0%), and were similar to comparator.

The most commonly reported unsolicited adverse events in the 28 days following the first or second dose of AFLURIA QUADRIVALENT in subjects 36 through 59 months of age were cough (7.7%), rhinorrhea (4.9%), pyrexia (3.7%), upper respiratory tract infection (2.5%), vomiting (2.1%), nasal congestion (1.6%), nasopharyngitis (1.7%), ororpharyngeal pain (1.2%), diarrhea (1.1%) and fatigue (1.1%), and were similar to the comparator.

No deaths were reported in Study 4. In the 180 days following vaccinations, AFLURIA QUADRIVALENT and comparator vaccine recipients experienced similar rates of serious adverse events (SAEs), none of which were related to study vaccines. No vaccine-related febrile seizures occurred in Study 4. Unrelated SAEs of febrile seizures occurred in two AFLURIA QUADRIVALENT recipients (6 through 35 months age group) at 43 and 104 days post-vaccinations.

Children 5 Years Through 17 Years of Age

Clinical safety data for AFLURIA QUADRIVALENT in older children and adolescents have been collected in one clinical trial, Study 5 (NCT02545543), a randomized, observer-blinded, comparator-controlled trial conducted in the U.S. in 2278 subjects aged 5 through 17 years. Subjects were stratified into one of two age cohorts of 5 through 8 years or 9 through 17 years (51.2% and 48.8% of the study population, respectively). The mean age of the population was 9.5 years, 52.1% were male, and racial groups consisted of 73.3% White, 20.7% Black, 0.8% Asian, 0.3% American Indian/Native American, and 0.7% Native Hawaiian/Pacific Islander; 23.8% of subjects were Hispanic/Latino. The mean ages of subjects 5 through 8 years and 9 through 17 years were 6.7 years and 12.5 years, respectively. Subjects in the safety population (N=2252) received either AFLURIA QUADRIVALENT (N=1692) or a U.S.-licensed comparator quadrivalent influenza vaccine (N=560). Study subjects were scheduled to receive either a single vaccination or two vaccinations 28 days apart based on their previous vaccination history. In this study, AFLURIA QUADRIVALENT and comparator vaccine were administered by needle and syringe (see Clinical Studies [14.5]).

Local (injection site) adverse reactions and systemic adverse reactions were solicited for 7 days post-vaccination. Cellulitis-like reactions (defined as concurrent Grade 3 pain, redness, and swelling/lump) at the injection site were monitored for 28 days post-vaccination. Subjects were instructed to report and return to clinic within 24 hours in the event of a cellulitis-like reaction. Unsolicited adverse events were collected for 28 days post-vaccination. All solicited local adverse reactions and systemic adverse reactions following any vaccination (first or second dose) are presented in Table 5.

Table 5: Proportion of Subjects Per Age Cohort with Any Solicited Local Adverse Reactions or Systemic Adverse Reactions within 7 Days after Administration of AFLURIA QUADRIVALENT or Comparator (Study 5) a
 | Percentage (%) b of Subjects in each Age Cohort Reporting a Reaction
 | Subjects 5 through 8 years |  |  |  | Subjects 9 through 17 years
 | AFLURIA Quadrivalent N=828-829 c |  | Comparator N=273-274 c |  | AFLURIA Quadrivalent N=790-792 c |  | Comparator N=261 c
 | Any | Gr 3 | Any | Gr 3 | Any | Gr 3 | Any | Gr 3
Local Adverse Reactions d
Pain | 51.3 | 0.8 | 49.6 | 0.7 | 51.5 | 0.3 | 45.2 | 0.4
Redness | 19.4 | 3.5 | 18.6 | 1.8 | 14.8 | 1.9 | 16.1 | 1.9
Swelling/Lump | 15.3 | 3.4 | 12.4 | 2.2 | 12.2 | 2.0 | 10.7 | 1.9
Systemic Adverse Reactions e
Headache | 12.3 | 0.1 | 10.6 | 0.4 | 18.8 | 0.4 | 14.6 | 0.4
Myalgia | 9.8 | 0.1 | 11.3 | 0.4 | 16.7 | 0.3 | 11.1 | 0.4
Malaise and Fatigue | 8.8 | 0.4 | 5.8 | 0 | 10.0 | 0.4 | 7.7 | 0
Nausea | 7.1 | 0.1 | 8.4 | 0 | 7.7 | 0 | 8.0 | 0
Diarrhea | 5.2 | 0 | 3.6 | 0 | 5.4 | 0 | 4.2 | 0
Fever | 4.5 | 1.2 | 3.6 | 0.7 | 2.1 | 0.5 | 0.8 | 0
Vomiting | 2.4 | 0.2 | 4.4 | 0 | 1.8 | 0 | 2.3 | 0
Abbreviations: Gr 3, Grade 3 (severe); Comparator, Comparator quadrivalent influenza vaccine [Fluarix® Quadrivalent (GlaxoSmithKline Biologicals)]
a NCT02545543
b Percent (%) is derived from the number of subjects that reported the reaction divided by the number of subjects in the Solicited Safety Population with non-missing data for each age cohort, treatment group, and each solicited parameter.
c N = number of subjects in the Solicited Safety Population (subjects who were vaccinated and provided any solicited safety data) for each study vaccine group.
d Local adverse reactions: Grade 3 pain is that which prevents daily activity; swelling/lump and redness: any = > 0mm diameter, Grade 3 = > 30mm diameter.
e Systemic adverse reactions: Fever: any = ≥ 100.4°F (Oral), Grade 3 = ≥ 102.2°F (Oral); Grade 3 for all other adverse reactions is that which prevents daily activity or requires significant medical intervention.

In subjects 5 through 8 years of age, all solicited local adverse reactions and systemic adverse reactions were reported at lower frequencies after the second vaccination than after the first vaccination with AFLURIA QUADRIVALENT with the exception of vomiting (which occurred at the same rate of 2.2% after each vaccination).

One subject, 8 years of age, experienced a cellulitis-like reaction at the injection site after vaccination with AFLURIA QUADRIVALENT.

The most commonly reported unsolicited adverse events in the 28 days following the first or second dose of AFLURIA QUADRIVALENT in subjects 5 through 8 years of age were cough (2.4%), pyrexia (1.8%), rhinorrhea (1.2%), and headache (1.0%), and were similar to the comparator.

For subjects ages 9 through 17 years who received AFLURIA QUADRIVALENT, the most commonly reported unsolicited adverse events in the 28 days following vaccination were oropharyngeal pain (1.6%), cough (1.3%), and upper respiratory tract infection (1.0%), and were similar to the comparator.

No deaths were reported in Study 5. In the 180 days following vaccinations, AFLURIA QUADRIVALENT and comparator vaccine recipients experienced similar rates of serious adverse events (SAEs). None of the SAEs appeared related to the study vaccines except for one case of influenza B infection (considered a vaccine failure) in an AFLURIA QUADRIVALENT recipient.

6.2 Postmarketing Experience

The following adverse reactions have been identified during post-approval use of AFLURIA or AFLURIA QUADRIVALENT. Because post-marketing reporting of adverse events is voluntary and from a population of uncertain size, it is not always possible to reliably estimate their frequency or establish a causal relationship to vaccine exposure. The adverse reactions have been included in this section based on strength of evidence for a causal relationship to AFLURIA or AFLURIA QUADRIVALENT, seriousness or frequency of reporting.

Blood and lymphatic system disorders

Thrombocytopenia

Immune system disorders

Allergic or immediate hypersensitivity reactions including anaphylactic shock and serum sickness

Nervous system disorders

Neuralgia, paresthesia, convulsions (including febrile seizures), dizziness, encephalomyelitis, encephalopathy, neuritis or neuropathy, transverse myelitis, GBS, syncope and presyncope

Vascular disorders

Vasculitis which may be associated with renal involvement

Musculoskeletal and Connective Tissue Disorders

Musculoskeletal pain and pain in the extremity

Skin and subcutaneous tissue disorders

Pruritus, urticaria, and rash

General disorders and administration site conditions

Cellulitis and large injection site swelling

Influenza-like illness, injected limb mobility decreased, pyrexia, injection site erythema and injection site reaction

8 USE IN SPECIFIC POPULATIONS

8.1 Pregnancy

Risk summary

All pregnancies have a risk of birth defect, loss, or other adverse outcomes. In the U.S. general population, the estimated background risk of major birth defects and miscarriage in clinically recognized pregnancies is 2% to 4% and 15% to 20%, respectively. Data collected prospectively in a Pregnancy Exposure Registry from individuals vaccinated with AFLURIA QUADRIVALENT revealed no evidence of vaccine-associated increase in the risk of major birth defects or miscarriages (see Data). Data for AFLURIA QUADRIVALENT are relevant to AFLURIA because both vaccines are manufactured using the same process and have overlapping compositions.

A developmental toxicity study of AFLURIA has been performed in female rats administered a single human dose [0.5 mL (divided)] of AFLURIA prior to mating and during gestation. This study revealed no evidence of harm to the fetus due to AFLURIA (see Data).

Clinical Considerations

Disease-associated Maternal and/or Embryo-Fetal Risk

Pregnant women are at increased risk for severe illness due to influenza compared to non-pregnant women. Pregnant women with influenza may be at increased risk for adverse pregnancy outcomes, including preterm labor and delivery.

Data

Human Data

Data from a Pregnancy Exposure Registry in the U.S. were prospectively collected from individuals vaccinated with AFLURIA QUADRIVALENT during 4 Northern Hemisphere influenza seasons (2017-18 through 2020-21). Of 483 individuals with known pregnancy outcomes 171, 201, and 111 were vaccinated during their 1st, 2nd, and 3rd trimester, respectively. Of 483 pregnancies, 477 resulted in live births, with 485 infants born. There were two stillbirths, neither associated with major birth defects, one each in individuals vaccinated in the first and second trimester. Among the 160 individuals enrolled in the study before 20 weeks gestation, there were four spontaneous abortions (2.5%). Among 171 individuals vaccinated in the 1st trimester, major birth defects were reported in two of 171 live born infants (1.2%). Among 201 individuals vaccinated in the 2nd trimester, major birth defects were reported in two of 203 live born infants (1.0%). The data generated from the pregnancy registry demonstrated rates of miscarriage and major birth defects that are consistent with estimated background rates.

Animal Data

In a developmental toxicity study, female rats were administered a single human dose [0.5 mL (divided)] of AFLURIA by intramuscular injection 21 days and 7 days prior to mating, and on gestation day 6. Some rats were administered an additional dose on gestation day 20. No vaccine-related fetal malformations or variations and no adverse effects on pre-weaning development were observed in the study.

8.2 Lactation

Risk Summary

It is not known whether AFLURIA is excreted in human milk. Data are not available to assess the effects of AFLURIA on the breastfed infant or on milk production/excretion.

The developmental and health benefits of breastfeeding should be considered along with the mother's clinical need for AFLURIA and any potential adverse effects on the breastfed child from AFLURIA or from the underlying maternal condition. For preventive vaccines, the underlying maternal condition is susceptibility to disease prevented by the vaccine.

8.4 Pediatric Use

The safety and effectiveness of AFLURIA in persons less than 6 months of age have not been established.

The PharmaJet Stratis Needle-Free Injection System is not approved as a method of administering AFLURIA to children and adolescents less than 18 years of age due to lack of adequate data supporting safety and effectiveness in this population.

8.5 Geriatric Use

In clinical studies, AFLURIA and AFLURIA QUADRIVALENT have been administered to, and safety information collected for, 870 and 867 subjects 65 years and older, respectively (see Clinical Trials Experience [6.1]). Among the 870 subjects 65 years and older who received AFLURIA, 539 were 65 through 74 years of age and 331 were 75 years of age and older. Among the 867 subjects who received AFLURIA QUADRIVALENT, 539 were 65 through 74 years of age and 328 were 75 years of age and older. After administration of AFLURIA and AFLURIA QUADRIVALENT, hemagglutination-inhibiting antibody responses in persons 65 years of age and older were lower than in younger adult subjects (see Clinical Studies [14.2]).

The PharmaJet Stratis Needle-Free Injection System is not approved as a method of administering AFLURIA to adults 65 years of age and older due to lack of adequate data supporting safety and effectiveness in this population.

11 DESCRIPTION

AFLURIA, Influenza Vaccine, is a sterile, clear, colorless to slightly opalescent injectable suspension for intramuscular use with some sediment that resuspends upon shaking to form a homogeneous suspension. AFLURIA is prepared from influenza viruses propagated in the allantoic fluid of embryonated chicken eggs. Following harvest, the viruses are purified in a sucrose density gradient using continuous flow zonal centrifugation. The purified viruses are inactivated with beta-propiolactone, and the virus particles are disrupted using sodium taurodeoxycholate to produce “split virions”. The disrupted viruses are further purified and suspended in a phosphate buffered isotonic solution.

AFLURIA is standardized according to USPHS requirements for the 2025-2026 influenza season and is formulated to contain 45 mcg hemagglutinin (HA) per 0.5 mL dose in the recommended ratio of 15 mcg HA for each of the three influenza strains recommended for the 2025-2026 Northern Hemisphere influenza season:

A/Victoria/4897/2022 IVR-238 (an A/Victoria/4897/2022 (H1N1)pdm09-like virus);

A/Croatia/10136RV/2023 X-425A (an A/Croatia/10136RV/2023 (H3N2)-like virus); and

B/Austria/1359417/2021 BVR-26 (a B/Austria/1359417/2021-like virus). A 0.25 mL dose contains 7.5 mcg HA of each of the same influenza strains.

Thimerosal, a mercury derivative, is not used in the manufacturing process for the single dose presentation. This presentation does not contain preservative. The multi-dose presentation contains thimerosal added as a preservative; each 0.5 mL dose contains 24.5 mcg of mercury and each 0.25 mL dose contains 12.25 mcg of mercury.

A single 0.5 mL dose of AFLURIA contains sodium chloride (4.1 mg), monobasic sodium phosphate (80 mcg), dibasic sodium phosphate (300 mcg), monobasic potassium phosphate (20 mcg), potassium chloride (20 mcg), and calcium chloride (0.5 mcg). From the manufacturing process, each 0.5 mL dose may also contain residual amounts of sodium taurodeoxycholate (≤ 10 ppm), ovalbumin (< 1 mcg), sucrose (< 10 mcg), neomycin sulfate (≤ 61.5 nanograms [ng]), polymyxin B (≤ 10.5 ng), beta-propiolactone (< 2.3 ng) and hydrocortisone (≤ 0.56 ng). A single 0.25 mL dose of AFLURIA contains half of these quantities.

The rubber tip cap and plunger used for the preservative-free, single-dose syringes and the rubber stoppers used for the multi-dose vial are not made with natural rubber latex.

12 CLINICAL PHARMACOLOGY

12.1 Mechanism of Action

Specific levels of hemagglutination inhibition (HI) antibody titers post-vaccination with inactivated influenza vaccine have not been correlated with protection from influenza virus. In some human studies, antibody titers of 1:40 or greater have been associated with protection from influenza illness in up to 50% of subjects.^2,3

Antibody against one influenza virus type or subtype confers limited or no protection against another. Furthermore, antibody to one antigenic variant of influenza virus might not protect against a new antigenic variant of the same type or subtype. Frequent development of antigenic variants through antigenic drift is the virologic basis for seasonal epidemics and the reason for the usual change to one or more new strains in each year's influenza vaccine.

13 NONCLINICAL TOXICOLOGY

13.1 Carcinogenesis, Mutagenesis, Impairment of Fertility

AFLURIA has not been evaluated for carcinogenic or mutagenic potential, or male infertility in animals.

14 CLINICAL STUDIES

14.1 Efficacy Against Laboratory-Confirmed Influenza

The efficacy of AFLURIA was demonstrated in Study 2, a randomized, observer-blind, placebo-controlled study conducted in 15,044 subjects. Healthy subjects 18 through 64 years of age were randomized in a 2:1 ratio to receive a single dose of AFLURIA (enrolled subjects: 10,033; evaluable subjects: 9,889) or placebo (enrolled subjects: 5,011; evaluable subjects: 4,960). The mean age of all randomized subjects was 35.5 years. 54.4% were female and 90.2% were White. Laboratory-confirmed influenza was assessed by active and passive surveillance of influenza-like illness (ILI) beginning 2 weeks post-vaccination until the end of the influenza season, approximately 6 months post-vaccination. ILI was defined as at least one respiratory symptom (e.g., cough, sore throat, nasal congestion) and at least one systemic symptom (e.g., oral temperature of 100.0ºF or higher, feverishness, chills, body aches). Nasal and throat swabs were collected from subjects who presented with an ILI for laboratory confirmation by viral culture and real-time reverse transcription polymerase chain reaction. Influenza virus strain was further characterized using gene sequencing and pyrosequencing.

Attack rates and vaccine efficacy, defined as the relative reduction in the influenza infection rate for AFLURIA compared to placebo, were calculated using the Per Protocol Population. Vaccine efficacy against laboratory-confirmed influenza infection due to influenza A or B virus strains contained in the vaccine was 60% with a lower limit of the 95% CI of 41% (Table 6).

Table 6: AFLURIA : Laboratory-Confirmed Influenza Infection Rate and Vaccine Efficacy in Adults 18 through 64 Years of Age (Study 2) a
 | Subjects b | Laboratory-Confirmed Influenza Cases | Influenza Infection Rate | Vaccine Efficacy c
 | N | N | n/N % | % | Lower Limit of the 95% CI
Vaccine-matched Strains
AFLURIA | 9889 | 58 | 0.59 | 60 | 41
Placebo | 4960 | 73 | 1.47 | 60 | 41
Any Influenza Virus Strain
AFLURIA | 9889 | 222 | 2.24 | 42 | 28
Placebo | 4960 | 192 | 3.87 | 42 | 28
Abbreviations: CI, confidence interval.
a NCT00562484
b The Per Protocol Population was identical to the Evaluable Population in this study.
c Vaccine efficacy = 1 minus the ratio of AFLURIA /placebo infection rates. The objective of the study was to demonstrate that the lower limit of the CI for vaccine efficacy was greater than 40%.

14.2 Immunogenicity in Adults and Older Adults Administered AFLURIA or AFLURIA QUADRIVALENT by Needle and Syringe

Study 1 was a randomized, double-blind, active-controlled trial conducted in the U.S. in adults aged 18 years of age and older. Subjects received one dose of either AFLURIA QUADRIVALENT (N=1691) or one of two formulations of AFLURIA (TIV-1 N=854 or TIV-2 N=850) each containing an influenza type B virus that corresponded to one of the two B viruses in AFLURIA QUADRIVALENT (a type B virus of the Yamagata lineage or a type B virus of the Victoria lineage, respectively). Data for AFLURIA QUADRIVALENT are relevant to AFLURIA because both vaccines are manufactured using the same process and have overlapping compositions.

Post-vaccination immunogenicity was evaluated on sera obtained 21 days after administration of a single dose of AFLURIA QUADRIVALENT or AFLURIA. The co-primary endpoints were HI Geometric Mean Titer (GMT) ratios (adjusted for baseline HI titers) and the difference in seroconversion rates for each vaccine strain, 21 days after vaccination. Pre-specified non-inferiority criteria required that the upper bound of the 2-sided 95% CI of the GMT ratio (AFLURIA/AFLURIA QUADRIVALENT) did not exceed 1.5 and the upper bound of the 2-sided 95% CI of the seroconversion rate difference (AFLURIA minus AFLURIA QUADRIVALENT) did not exceed 10.0% for each strain.

Serum HI antibody responses to AFLURIA QUADRIVALENT were non-inferior to both AFLURIA formulations for all influenza strains for subjects 18 years of age and older. Additionally, non-inferiority was demonstrated for both endpoints in both age sub-groups, adults aged 18 through 64 years and 65 years and older, for all strains (Table 7). Superiority of the immune response to each of the influenza B strains contained in AFLURIA QUADRIVALENT was shown relative to the antibody response after vaccination with both AFLURIA formulations not containing that B lineage strain for subjects 18 years of age and older. Superiority against the alternate B strain was also demonstrated for each of the influenza B strains in both age sub-groups; 18 through 64 years and 65 years and older. Post-hoc analyses of immunogenicity endpoints by gender did not demonstrate meaningful differences between males and females. The study population was not sufficiently diverse to assess differences between races or ethnicities.

Table 7: Post-Vaccination HI Antibody GMTs, Seroconversion Rates, and Analyses of Non-Inferiority of AFLURIA QUADRIVALENT Relative to AFLURIA by Age Cohort (Study 1) a
 | Post-vaccination GMT |  | GMT Ratio b | Seroconversion % c |  | Difference | Met both pre-defined non-inferiority criteria? d
Strain | AFLURIA Quadrivalent | Pooled AFLURIA or AFLURIA (TIV-1 B Yamagata) or AFLURIA (TIV-2 B Victoria) | Pooled AFLURIA or AFLURIA TIV-1 or AFLURIA TIV-2 over AFLURIA Quadrivalent (95% CI) | AFLURIA Quadrivalent N=1691 | Pooled AFLURIA or AFLURIA (TIV-1 B Yamagata) or AFLURIA (TIV-2 B Victoria) | Pooled AFLURIA or AFLURIA TIV-1 or AFLURIA TIV-2 minus AFLURIA Quadrivalent (95% CI) | Met both pre-defined non-inferiority criteria? d
18 through 64 years | AFLURIA Quadrivalent N=835, Pooled AFLURIA N=845, AFLURIA (TIV-1) N=424, AFLURIA (TIV-2) N=421
A(H1N1) | 432.7 | 402.8 | 0.93 e (0.85, 1.02) | 51.3 | 49.1 | -2.1 h (-6.9, 2.7) | Yes
A(H3N2) | 569.1 | 515.1 | 0.91 e (0.83, 0.99) | 56.3 | 51.7 | -4.6 h (-9.4, 0.2) | Yes
B/Massachusetts/ 2/2012 (B Yamagata) | 92.3 | 79.3 | 0.86 f (0.76, 0.97) | 45.7 | 41.3 | -4.5 i (-10.3, 1.4) | Yes
B/Brisbane/ 60/2008 (B Victoria) | 110.7 | 95.2 | 0.86 g (0.76, 0.98) | 57.6 | 53.0 | -4.6 j (-10.5, 1.2) | Yes
≥ 65 years | AFLURIA Quadrivalent N=856, Pooled AFLURIA N=859, AFLURIA (TIV-1) N=430, AFLURIA (TIV-2) N=429
A(H1N1) | 211.4 | 199.8 | 0.95 e (0.88, 1.02) | 26.6 | 26.4 | -0.2 h (-5.0, 4.5) | Yes
A(H3N2) | 419.5 | 400.0 | 0.95 e (0.89, 1.02) | 25.9 | 27.0 | 1.1 h (-3.7, 5.8) | Yes
B/Massachusetts/ 2/2012 (B Yamagata) | 43.3 | 39.1 | 0.90 f (0.84, 0.97) | 16.6 | 14.4 | -2.2 i (-8.0, 3.6) | Yes
B/Brisbane/ 60/2008 (B Victoria) | 66.1 | 68.4 | 1.03 g (0.94, 1.14) | 23.5 | 24.7 | 1.2 j (-4.6, 7.0) | Yes
Abbreviations: CI, confidence interval; GMT, geometric mean titer.
a NCT02214225
b GMT ratio was computed after fitting a multi-variable model on the post-vaccination titers including sex, vaccination history, pre-vaccination HI titers and other factors.
c Seroconversion rate is defined as a 4-fold increase in post-vaccination HI antibody titer from pre-vaccination titer ≥ 1:10 or an increase in titer from < 1:10 to ≥ 1:40.
d Non-inferiority (NI) criterion for the GMT ratio: upper bound of 2-sided 95% CI on the GMT ratio of Pooled AFLURIA or AFLURIA (TIV-1 B Yamagata) or AFLURIA (TIV-2 B Victoria)/AFLURIA Quadrivalent should not exceed 1.5. NI criterion for the SCR difference: upper bound of 2-sided 95% CI on the difference between SCR Pooled AFLURIA or AFLURIA (TIV-1 B Yamagata) or AFLURIA (TIV-2 B Victoria) minus AFLURIA Quadrivalent should not exceed 10%.
e Pooled AFLURIA /AFLURIA Quadrivalent
f AFLURIA (TIV-1 B Yamagata)/AFLURIA Quadrivalent
g AFLURIA (TIV-2 B Victoria)/AFLURIA Quadrivalent
h Pooled AFLURIA – AFLURIA Quadrivalent
i AFLURIA (TIV-1 B Yamagata) - AFLURIA Quadrivalent
j AFLURIA (TIV-2 B Victoria) - AFLURIA Quadrivalent

14.3 Immunogenicity in Adults Administered AFLURIA by PharmaJet Stratis Needle-Free Injection System

Study 3 was a randomized, comparator-controlled, non-inferiority study that enrolled 1,250 subjects 18 through 64 years of age. This study compared the immune response following administration of AFLURIA when delivered intramuscularly using either the PharmaJet Stratis Needle-Free Injection System or needle and syringe. Immunogenicity assessments were performed prior to vaccination and at 28 days after vaccination in the immunogenicity population (1130 subjects, 562 PharmaJet Stratis Needle-Free Injection System group, 568 needle and syringe group). The co-primary endpoints were HI GMT ratios for each vaccine strain and the absolute difference in seroconversion rates for each vaccine strain 28 days after vaccination. As shown in Table 8, non-inferiority of administration of AFLURIA by the PharmaJet Stratis Needle-Free Injection System compared to administration of AFLURIA by needle and syringe was demonstrated in the immunogenicity population for all strains. Post-hoc analyses of immunogenicity by age showed that younger subjects (18 through 49 years) elicited higher immunological responses than older subjects (50 through 64 years). Post-hoc analyses of immunogenicity according to sex and body mass index did not reveal significant influences of these variables on immune responses. The study population was not sufficiently diverse to assess immunogenicity by race or ethnicity.

Table 8: Baseline and Post-Vaccination HI Antibody GMTs, Seroconversion Rates, and Analyses of Non-Inferiority of AFLURIA Administered by PharmaJet Stratis Needle-Free Injection System or Needle and Syringe, Adults 18 through 64 Years of Age (Study 3) a
 | Baseline GMT |  | Post-vaccination GMT |  | GMT Ratio b | Seroconversion % c |  | Difference | Met both pre-defined non-inferiority criteria? d
Strain | Needle and Syringe N=568 | PharmaJet Stratis Needle-Free Injection System N=562 | Needle and Syringe N=568 | PharmaJet Stratis Needle-Free Injection System N=562 | Needle and Syringe over PharmaJet Stratis Needle-Free Injection System (95% CI) | Needle and Syringe N=568 | PharmaJet Stratis Needle-Free Injection System N=562 | Needle and Syringe minus PharmaJet Stratis Needle-Free Injection System (95% CI) | Met both pre-defined non-inferiority criteria? d
A(H1N1) | 79.5 | 83.7 | 280.6 | 282.9 | 0.99 (0.88, 1.12) | 38.4 | 37.5 | 0.8 (-4.8, 6.5) | Yes
A(H3N2) | 75.4 | 68.1 | 265.9 | 247.3 | 1.08 (0.96, 1.21) | 45.1 | 43.8 | 1.3 (-4.5, 7.1) | Yes
B | 12.6 | 13.5 | 39.7 | 42.5 | 0.94 (0.83, 1.06) | 35.2 | 34.9 | 0.3 (-5.2, 5.9) | Yes
Abbreviations: CI, confidence interval; GMT, geometric mean titer.
a NCT01688921
b GMT ratio is defined as post-vaccination GMT for Needle and Syringe/PharmaJet Stratis Needle-Free Injection System.
c Seroconversion rate is defined as a 4-fold increase in post-vaccination HI antibody titer from pre-vaccination titer ≥ 1:10 or an increase in titer from < 1:10 to ≥ 1:40.
d Non-inferiority (NI) criterion for the GMT ratio: upper bound of 2-sided 95% CI on the GMT ratio of Needle and Syringe/PharmaJet Stratis Needle-Free Injection System should not exceed 1.5. NI criterion for the seroconversion rate (SCR) difference: upper bound of 2-sided 95% CI on the difference between SCR Needle and Syringe – SCR PharmaJet Stratis Needle-Free Injection System should not exceed 10%.

14.4 Immunogenicity in Children 6 Months through 59 Months Administered AFLURIA QUADRIVALENT by Needle and Syringe

Study 4 was a randomized, observer-blind, comparator-controlled trial conducted in the U.S. in children 6 months through 59 months of age. A total of 2247 subjects were randomized 3:1 to receive AFLURIA QUADRIVALENT (N=1684) or a U.S.-licensed comparator quadrivalent influenza vaccine (N=563). Children 6 months through 35 months received one or two 0.25 mL doses and children 36 months through 59 months received one or two 0.5 mL doses. Subjects were eligible to receive a second dose at least 28 days after the first dose depending on their influenza vaccination history, consistent with the 2016-2017 recommendations of the Advisory Committee on Immunization Practices (ACIP) for Prevention and Control of Seasonal Influenza with Vaccines. Approximately 40% of subjects in each treatment group received two vaccine doses. Data for AFLURIA QUADRIVALENT are relevant to AFLURIA because both vaccines are manufactured using the same process and have overlapping compositions.

Baseline serology for HI assessment was collected prior to vaccination. Postvaccination immunogenicity was evaluated by HI assay on sera obtained 28 days after the last vaccination dose.

The primary objective was to demonstrate that vaccination with AFLURIA QUADRIVALENT elicits an immune response that is not inferior to that of a comparator vaccine containing the same recommended virus strains. The Per Protocol Population (AFLURIA QUADRIVALENT n=1456, Comparator QIV n=484) was used for the primary endpoint analyses. The co-primary endpoints were HI Geometric Mean Titer (GMT) ratios (adjusted for baseline HI titers and other covariates) and seroconversion rates for each vaccine strain, 28 days after the last vaccination. Pre-specified non-inferiority criteria required that the upper bound of the 2-sided 95% CI of the GMT ratio (Comparator QIV/AFLURIA QUADRIVALENT) did not exceed 1.5 and the upper bound of the 2-sided 95% CI of the seroconversion rate difference (Comparator QIV minus AFLURIA QUADRIVALENT) did not exceed 10.0% for each strain. Serum HI antibody responses to AFLURIA QUADRIVALENT were non-inferior for both GMT ratio and seroconversion rates relative to the comparator vaccine for all influenza strains (Table 9). Analyses of immunogenicity endpoints by gender did not demonstrate meaningful differences between males and females. The study population was not sufficiently diverse to assess differences among races or ethnicities.

Table 9: Post-Vaccination HI Antibody GMTs, SCRs, and Analyses of Non-Inferiority of AFLURIA QUADRIVALENT Relative to a U.S.-Licensed Comparator Quadrivalent Influenza Vaccine for each Strain 28 Days after Last Vaccination Among a Pediatric Population 6 through 59 Months of Age (Per Protocol Population) (Study 4) a,b
 | Post-vaccination GMT |  | GMT Ratio c | Seroconversion % d |  | SCR Difference e | Met both pre-defined non-inferiority criteria? f
Strain | AFLURIA Quadrivalent N=1456 | Comparator N=484 | Comparator over AFLURIA Quadrivalent (95% CI) | AFLURIA Quadrivalent N=1456 (95% CI) | Comparator N=484 (95% CI) | Comparator minus AFLURIA Quadrivalent (95% CI) | Met both pre-defined non-inferiority criteria? f
A(H1N1) | 353.5 (n=1455 g) | 281.0 (n=484) | 0.79 (0.72, 0.88) | 79.1 (76.9, 81.1) (n=1456) | 68.8 (64.5, 72.9) (n=484) | -10.3 (-15.4, -5.1) | Yes
A(H3N2) | 393.0 (n=1454 gi) | 500.5 (n=484) | 1.27 (1.15, 1.42) | 82.3 (80.2, 84.2) (n=1455 i) | 84.9 (81.4, 88.0) (n=484) | 2.6 (-2.5, 7.8) | Yes
B/Phuket/3073/ 2013 (B Yamagata) | 23.7 (n=1455 g) | 26.5 (n=484) | 1.12 (1.01, 1.24) | 38.9 (36.4, 41.4) (n=1456) | 41.9 (37.5, 46.5) (n=484) | 3.1 (-2.1, 8.2) | Yes
B/Brisbane/60/ 2008 (B Victoria) | 54.6 (n=1455 g) | 52.9 (n=483h) | 0.97 (0.86, 1.09) | 60.2 (57.6, 62.7) (n=1456) | 61.1 (56.6, 65.4) (n=483 h) | 0.9 (-4.2, 6.1) | Yes
Abbreviations: CI, confidence interval; Comparator, Comparator quadrivalent influenza vaccine (Fluzone Quadrivalent [Sanofi Aventis]); GMT (adjusted), geometric mean titer; SCR, seroconversion rate.
a NCT02914275
b The Per-Protocol Population comprised all subjects (6 through 35 months of age receiving one or two 0.25 mL doses and 36 through 59 months of age receiving one or two 0.5 mL doses) in the Evaluable Population who did not have any protocol deviations that were medically assessed as potentially impacting on immunogenicity results.
c GMT Ratio = Comparator / AFLURIA QUADRIVALENT. Adjusted analysis model: Log-transformed Post-Vaccination HI Titer=Vaccine + Age Cohort [6 through 35 months or 36 through 59 months] + Gender + Vaccination History [y/n] + Log-transformed Pre-Vaccination HI Titer + Site + Number of Doses (1 vs 2) + Age Cohort*Vaccine. The Age Cohort*Vaccine interaction term was excluded from the model fit for the strains A(H1N1), A(H3N2) and B/Yamagata as the interaction result was non-significant (p>0.05). Least square means were back transformed.
d Seroconversion rate was defined as the percentage of subjects with either a prevaccination HI titer < 1:10 and a postvaccination HI titer ≥ 1:40 or a prevaccination HI titer ≥ 1:10 and a 4-fold increase in postvaccination HI titer.
e Seroconversion rate difference = Comparator SCR percentage minus AFLURIA QUADRIVALENT SCR percentage.
f Noninferiority (NI) criterion for the GMT ratio: upper bound of two-sided 95% CI on the GMT ratio of Comparator / AFLURIA QUADRIVALENT should not exceed 1.5. NI criterion for the SCR difference: upper bound of two-sided 95% CI on the difference between SCR Comparator – AFLURIA QUADRIVALENT should not exceed 10%.
g Subject 8400402-0073 was excluded from the Per-Protocol Population for the adjusted GMT analysis for the GMT ratio because the subject did not have information on all covariates (unknown prevaccination history).
h Subject 8400427-0070 had missing B/Victoria Antigen pre-vaccination titer.
iSubject 8400402-0074 had missing A/H3N2 post-vaccination titer.

14.5 Immunogenicity in Children 5 through 17 Years Administered AFLURIA QUADRIVALENT by Needle and Syringe

Study 5 was a randomized, observer-blinded, comparator-controlled trial conducted in the U.S. in children 5 through 17 years of age. A total of 2278 subjects were randomized 3:1 to receive one or two doses of AFLURIA QUADRIVALENT (N=1709) or a U.S.-licensed comparator quadrivalent influenza vaccine (N=569). Subjects 5 through 8 years of age were eligible to receive a second dose at least 28 days after the first dose depending on their influenza vaccination history, consistent with the 2015-2016 recommendations of the Advisory Committee on Immunization Practices (ACIP) for Prevention and Control of Seasonal Influenza with Vaccines. Approximately 25% of subjects in each treatment group in the 5 through 8 years of age sub-group received two vaccine doses. Data for AFLURIA QUADRIVALENT are relevant to AFLURIA because both vaccines are manufactured using the same process and have overlapping compositions.

Baseline serology for HI assessment was collected prior to vaccination. Post-vaccination immunogenicity was evaluated by HI assay on sera obtained 28 days after the last vaccination dose.

The primary objective was to demonstrate that vaccination with AFLURIA QUADRIVALENT elicits an immune response that is not inferior to that of a comparator vaccine containing the same recommended virus strains. The Per Protocol Population (AFLURIA QUADRIVALENT n=1605, Comparator n=528) was used for the primary endpoint analyses. The co-primary endpoints were HI Geometric Mean Titer (GMT) ratios (adjusted for baseline HI titers and other covariates) and seroconversion rates for each vaccine strain, 28 days after the last vaccination. Pre-specified non-inferiority criteria required that the upper bound of the 2-sided 95% CI of the GMT ratio (Comparator/AFLURIA QUADRIVALENT) did not exceed 1.5 and the upper bound of the 2-sided 95% CI of the seroconversion rate difference (Comparator minus AFLURIA QUADRIVALENT) did not exceed 10.0% for each strain. Serum HI antibody responses to AFLURIA QUADRIVALENT were non-inferior for both GMT ratio and seroconversion rates relative to the comparator vaccine for all influenza strains (Table 10). Analyses of immunogenicity endpoints by gender did not demonstrate meaningful differences between males and females. The study population was not sufficiently diverse to assess differences among races or ethnicities.

Table 10:Post-Vaccination HI Antibody GMTs, SCRs, and Analyses of Non-Inferiority of AFLURIA QUADRIVALENT Relative to a U.S.-Licensed Comparator Quadrivalent Influenza Vaccine for each Strain 28 Days after Last Vaccination Among a Pediatric Population 5 through 17 Years of Age (Per Protocol Population) (Study 5) a,b
 | Post-vaccination GMT |  | GMT Ratio c | Seroconversion % d |  | SCR Difference e | Met both pre-defined non-inferiority criteria? f
Strain | AFLURIA Quadrivalent N=1605 | Comparator N=528 | Comparator over AFLURIA Quadrivalent (95% CI) | AFLURIA Quadrivalent N=1605 (95% CI) | Comparator N=528 (95% CI) | Comparator minus AFLURIA Quadrivalent (95% CI) | Met both pre-defined non-inferiority criteria? f
A(H1N1) | 952.6 (n=1604 g) | 958.8 | 1.01 (0.93, 1.09) | 66.4 (64.0, 68.7) | 63.3 (59.0, 67.4) | -3.1 (-8.0, 1.8) | Yes
A(H3N2) | 886.4 (n=1604 g) | 930.6 | 1.05 (0.96, 1.15) | 82.9 (81.0, 84.7) | 83.3 (79.9, 86.4) | 0.4 (-4.5, 5.3) | Yes
B/Phuket/3073/ 2013 (B Yamagata) | 60.9 (n=1604 g) | 54.3 | 0.89 (0.81, 0.98) | 58.5 (56.0, 60.9) | 55.1 (50.8, 59.4) | -3.4 (-8.3, 1.5) | Yes
B/Brisbane/60/ 2008 (B Victoria) | 145.0 (n=1604 g) | 133.4 | 0.92 (0.83, 1.02) | 72.1 (69.8, 74.3) | 70.1 (66.0, 74.0) | -2.0 (-6.9, 2.9) | Yes
Abbreviations: CI, confidence interval; Comparator, Comparator quadrivalent influenza vaccine (Fluarix® Quadrivalent [GlaxoSmithKline Biologicals]); GMT (adjusted), geometric mean titer; SCR, seroconversion rate.
a NCT02545543
b The Per-Protocol Population comprised all subjects in the Evaluable Population who did not have any protocol deviations that were medically assessed as potentially impacting on immunogenicity results.
c GMT Ratio = Comparator /AFLURIA QUADRIVALENT. Adjusted analysis model: Log-transformed Post-Vaccination HI Titer=Vaccine + Age Strata [5-8, 9-17] + Gender + Vaccination History [y/n] + Log-transformed Pre-Vaccination HI Titer + Site + Number of Doses (1 vs 2) + Age Strata*Vaccine. The Age Strata*Vaccine interaction term was excluded from the model fit for the strains B/Yamagata and B/Victoria as the interaction result was non-significant (p>0.05). Least square means were back transformed.
d Seroconversion rate was defined as the percentage of subjects with either a prevaccination HI titer < 1:10 and a postvaccination HI titer ≥ 1:40 or a prevaccination HI titer ≥ 1:10 and a 4-fold increase in postvaccination HI titer.
e Seroconversion rate difference = Comparator SCR percentage minus AFLURIA QUADRIVALENT SCR percentage.
f Non-inferiority (NI) criterion for the GMT ratio: upper bound of two-sided 95% CI on the GMT ratio of Comparator /AFLURIA QUADRIVALENT should not exceed 1.5. NI criterion for the SCR difference: upper bound of two-sided 95% CI on the difference between SCR Comparator – AFLURIA QUADRIVALENT should not exceed 10%.
g Subject 8400394-0046 was excluded from the Per-Protocol Population for the adjusted GMT analysis for the GMT ratio since the subject did not have information on all covariates (unknown prevaccination history).

15 REFERENCES

1. Centers for Disease Control and Prevention. Prevention and Control of Influenza: Recommendations of the Advisory Committee on Immunization Practices (ACIP). MMWR Recomm Rep 2010;59 (RR-8):1-62.
2. Hannoun C, Megas F, Piercy J. Immunogenicity and Protective Efficacy of Influenza Vaccination. Virus Res 2004;103:133-138.
3. Hobson D, Curry RL, Beare AS, et al. The Role of Serum Hemagglutination-Inhibiting Antibody in Protection against Challenge Infection with Influenza A2 and B Viruses. J Hyg Camb 1972;70:767-777.

16 HOW SUPPLIED/STORAGE AND HANDLING

16.1 How Supplied

Each product presentation includes a package insert and the following components:

Presentation | Carton NDC Number | Components
Pre-Filled Syringe | 33332-025-03 | - Ten 0.5 mL single-dose syringes fitted with a Luer-Lok™ attachment without needles [NDC 33332-025-04]
Multi-Dose Vial | 33332-125-10 | - One 5 mL vial [NDC 33332-125-11]

16.2 Storage and Handling

- Store refrigerated at 2-8°C (36-46°F).
- Do not freeze. Discard if product has been frozen.
- Protect from light.
- Do not use AFLURIA beyond the expiration date printed on the label.
- Between uses, return the multi-dose vial to the recommended storage conditions.
- Once the stopper of the multi-dose vial has been pierced the vial must be discarded within 28 days.
- The number of needle punctures must not exceed 20 per multi-dose vial.

17 PATIENT COUNSELING INFORMATION

- Inform the vaccine recipient or guardian of the potential benefits and risks of immunization with AFLURIA.
- Inform the vaccine recipient or guardian that AFLURIA is an inactivated vaccine that cannot cause influenza but stimulates the immune system to produce antibodies that protect against influenza, and that the full effect of the vaccine is generally achieved approximately 3 weeks after vaccination.
- Instruct the vaccine recipient or guardian to report any severe or unusual adverse reactions to their healthcare provider.
- Provide the vaccine recipient Vaccine Information Statements prior to immunization. These materials are available free of charge at the Centers for Disease Control and Prevention (CDC) website (www.cdc.gov/vaccines).
- Instruct the vaccine recipient that annual revaccination is recommended.

Manufactured by:
Seqirus Pty Ltd. Parkville, Victoria, 3052, Australia
U.S. License No. 2044

Distributed by:
Seqirus USA Inc. 25 Deforest Avenue, Summit, NJ 07901, USA
1-855-358-8966

AFLURIA and AFLURIA QUADRIVALENT are registered trademarks of Seqirus UK Limited or its affiliates.

PharmaJet® and Stratis® are trademarks of PharmaJet Inc.

Luer-Lok™ is a trademark of Becton, Dickinson and Company Corporation.

Principal Display Panel – 5 mL Carton Label

NDC 33332-125-10

Influenza Vaccine
afluria®

2025 - 2026 Formula

For use in persons 6 months
and older

FOR INTRAMUSCULAR USE

5 mL Multi-dose Vial

Rx Only

Seqirus™

Principal Display Panel – 5 mL Vial Label

NDC 33332-125-11

Influenza Vaccine
afluria®
2025-2026 Formula

5 mL Multi-dose Vial

FOR IM USE Rx only

Principal Display Panel – 0.5 mL Carton Label

NDC 33332-025-03

Influenza Vaccine
afluria®

2025 - 2026 Formula

For use in persons 3 years and older

FOR INTRAMUSCULAR USE

10 Pre-Filled Syringes
each containing a single 0.5 mL dose

Rx Only

Seqirus™

Principal Display Panel – 0.5 mL Vial Label

NDC 33332-025-04

Influenza Vaccine
afluria®
2025-2026 Formula